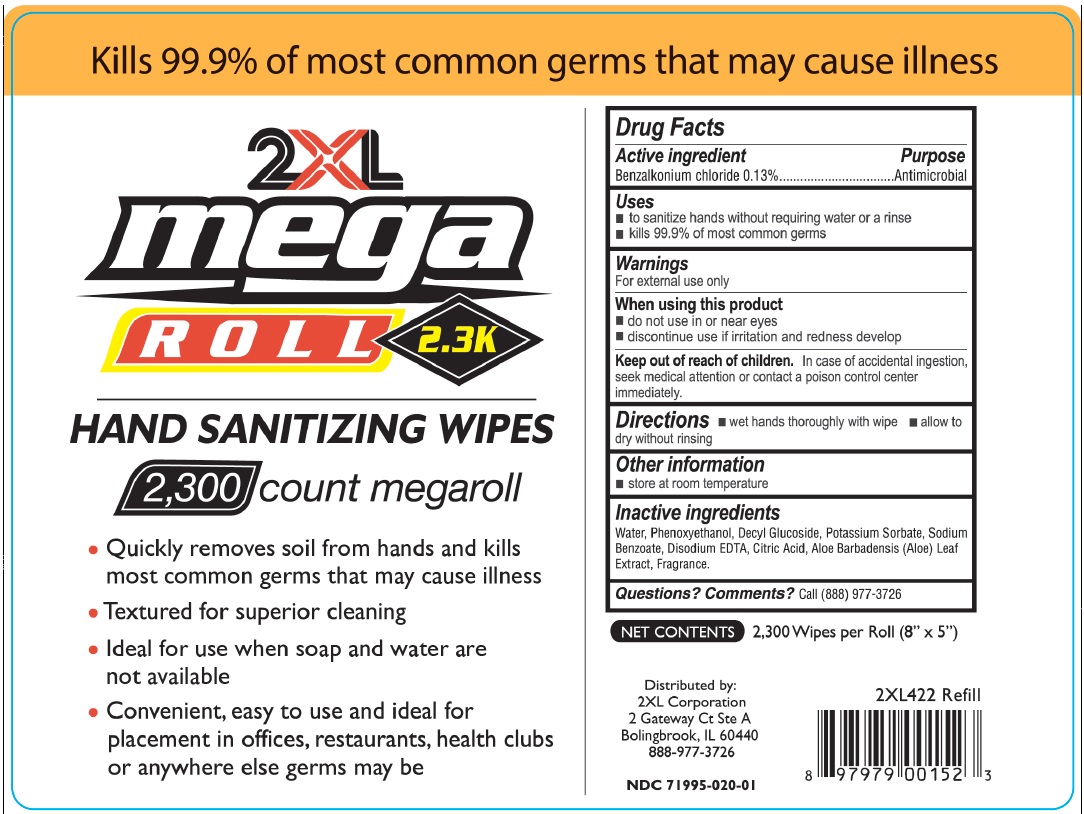 DRUG LABEL: 2XL Mega Rolls Sanitizing Wipes
NDC: 71995-020 | Form: SWAB
Manufacturer: 2xl Corporation
Category: otc | Type: HUMAN OTC DRUG LABEL
Date: 20251205

ACTIVE INGREDIENTS: BENZALKONIUM CHLORIDE 0.13 g/100 g
INACTIVE INGREDIENTS: WATER; PHENOXYETHANOL; DECYL GLUCOSIDE; POTASSIUM SORBATE; SODIUM BENZOATE; EDETATE DISODIUM; CITRIC ACID MONOHYDRATE; ALOE VERA LEAF

Drug Facts

Active ingredient

Benzalkonium chloride 0.13%

Purpose

Antimicrobial

Uses

- to sanitize hands without requiring water or a rinse
- kills 99.9% of most common germs

Warnings

For external use only

When using this product

- do not use in or near the eye
- discontinue use if irritation and redness develop

Keep out of reach of children

In case of accidental ingestion, seek medical attention or contact a Poison Control Center immediately.

Directions

- wet hands thoroughly with wipe
- allow to dry without rinsing

Other information

Store at room temperature

Inactive ingredients

Water, Phenoxyethanol, Decyl Glucoside, Potassium Sorbate, Sodium Benzoate, Disodium EDTA, Citric Acid, Aloe Barbadensis (Aloe) Leaf Extract, Fragrance

Questions? Comments?

Call (888)977-3726

Principal Display Panel

NDC 71995-020-01

Kills 99.9% of most common germs that may cause illness

2XL Mega ROLL

2.3K

SANITIZING WIPES

2300 count megaroll

- Quickly removes soil and kills most common germs that may cause illness
- Textured for superior cleaning
- Sanitizes hand while cleaning effectively
- Convenient, easy to use and ideal for placement in offices, restaurants, health clubs, or anywhere else germs may be

NET CONTENTS 2300 Wipes per Roll (8'' X 5'')

Net Weight: 5460g/roll